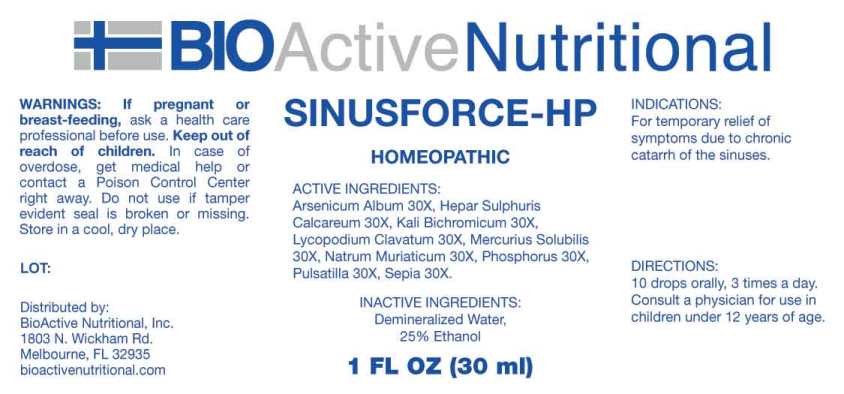 DRUG LABEL: Sinusforce-HP
NDC: 43857-0585 | Form: LIQUID
Manufacturer: BioActive Nutritional, Inc.
Category: homeopathic | Type: HUMAN OTC DRUG LABEL
Date: 20240912

ACTIVE INGREDIENTS: ARSENIC TRIOXIDE 30 [hp_X]/1 mL; CALCIUM SULFIDE 30 [hp_X]/1 mL; POTASSIUM DICHROMATE 30 [hp_X]/1 mL; LYCOPODIUM CLAVATUM SPORE 30 [hp_X]/1 mL; MERCURIUS SOLUBILIS 30 [hp_X]/1 mL; SODIUM CHLORIDE 30 [hp_X]/1 mL; PHOSPHORUS 30 [hp_X]/1 mL; PULSATILLA PRATENSIS WHOLE 30 [hp_X]/1 mL; SEPIA OFFICINALIS JUICE 30 [hp_X]/1 mL
INACTIVE INGREDIENTS: WATER; ALCOHOL

DRUG FACTS:

ACTIVE INGREDIENTS:

Arsenicum Album 30X, Hepar Sulphuris Calcareum 30X, Kali Bichromicum 30X, Lycopodium Clavatum 30X, Mercurius Solubilis 30X, Natrum Muriaticum 30X, Phosphorus 30X, Pulsatilla (Pratensis) 30X, Sepia 30X.

INDICATIONS:

For temporary relief of symptoms due to chronic catarrh of sinuses.

WARNINGS:

If pregnant or breast-feeding, ask a health care professional before use.

Keep out of reach of children. In case of overdose, get medical help or contact a Poison Control Center right away.

Do not use if tamper evident seal is broken or missing.

Store in cool, dry place.

KEEP OUT OF REACH OF CHILDREN:

In case of overdose, get medical help or contact a Poison Control Center right away.

DIRECTIONS:

10 drops orally, 3 times a day. Consult a physician for use in children under 12 years of age.

INDICATIONS:

For temporary relief of symptoms due to chronic catarrh of sinuses.

INACTIVE INGREDIENTS:

Demineralized Water, 25% Ethanol

QUESTIONS:

Distributed by:
BioActive Nutritional, Inc.
1803 N. Wickham Rd.
Melbourne, FL 32935
bioactivenutritional.com

PACKAGE LABEL DISPLAY:

BIOActive Nutritional

SINUSFORCE-HP

HOMEOPATHIC

1 FL OZ (30 ml)